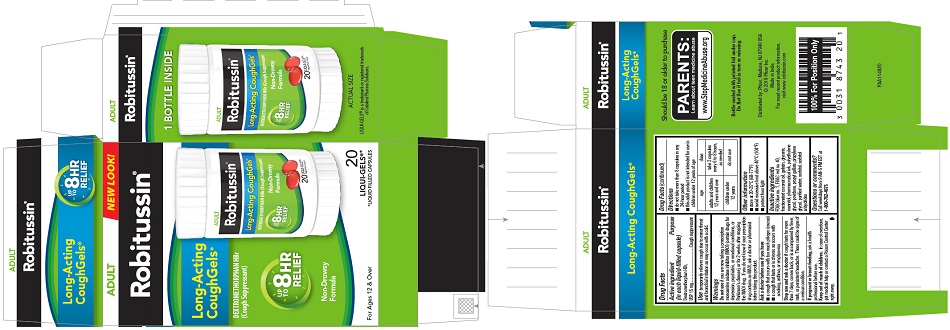 DRUG LABEL: ROBITUSSIN LONG-ACTING COUGHGELS
NDC: 0031-8743 | Form: CAPSULE, LIQUID FILLED
Manufacturer: Haleon US Holdings LLC
Category: otc | Type: HUMAN OTC DRUG LABEL
Date: 20240319

ACTIVE INGREDIENTS: DEXTROMETHORPHAN HYDROBROMIDE 15 mg/1 1
INACTIVE INGREDIENTS: FD&C BLUE NO. 1; FD&C RED NO. 40; COCONUT OIL; GELATIN, UNSPECIFIED; GLYCERIN; MANNITOL; POLYETHYLENE GLYCOL, UNSPECIFIED; POVIDONE, UNSPECIFIED; PROPYL GALLATE; PROPYLENE GLYCOL; WATER; SORBITOL

Drug Facts

Active ingredient (in each liquid-filled capsule)

Dextromethorphan HBr, USP 15 mg

Purpose

Cough suppressant

Use

temporarily relieves cough due to minor throat and bronchial irritation as may occur with a cold.

Warnings

DO NOT USE

Do not useif you are now taking a prescription monoamine oxidase inhibitor (MAOI) (certain drugs for depression, psychiatric, or emotional conditions, or Parkinson's disease), or for 2 weeks after stopping the MAOI drug. If you do not know if your prescription drug contains an MAOI, ask a doctor or pharmacist before taking this product.

Ask a doctor before use if you have

- a cough that occurs with too much phlegm (mucus)
- a cough that lasts or is chronic as occurs with smoking, asthma, or emphysema

Stop use and ask a doctor ifcough lasts for more than 7 days, comes back, or is accompanied by fever, rash, or persistent headache. These could be signs of a serious condition.

PREGNANCY OR BREAST FEEDING

If pregnant or breast-feeding,ask a health professional before use.

Keep out of reach of children.In case of overdose, get medical help or contact a Poison Control Center right away.

Directions

- do not take more than 8 capsules in any 24-hour period
- this adult product is not intended for use in children under 12 years of age

age |  | dose
adults and children 12 years and over |  | take 2 capsules every 6 to 8 hours, as needed
children under 12 years |  | do not use

Other information

- store at 20-25°C (68-77°F)
- avoid excessive heat above 40°C (104°F)
- protect from light

Inactive ingredients

FD&C blue no. 1, FD&C red no. 40, fractionated coconut oil, gelatin, glycerin, mannitol, pharmaceutical ink, polyethylene glycol, povidone, propyl gallate, propylene glycol, purified water, sorbitol, sorbitol anhydrides

Questions or comments?

Call weekdays from 9 AM-5 PM EST at 1-800-762-4675

Distributed by: Pfizer, Madison, NJ 07940 USA

PRINCIPAL DISPLAY PANEL

ADULT
NEW LOOK!

Robitussin®

Long-Acting
CoughGels®

DEXTROMETHORPHAN HBr
(Cough Suppressant)

UP
TO
8 HR
RELIEF

Non-Drowsy
Formula

For Ages 12 & Over

20
LIQUI-GELS®*
*LIQUID FILLED CAPSULES